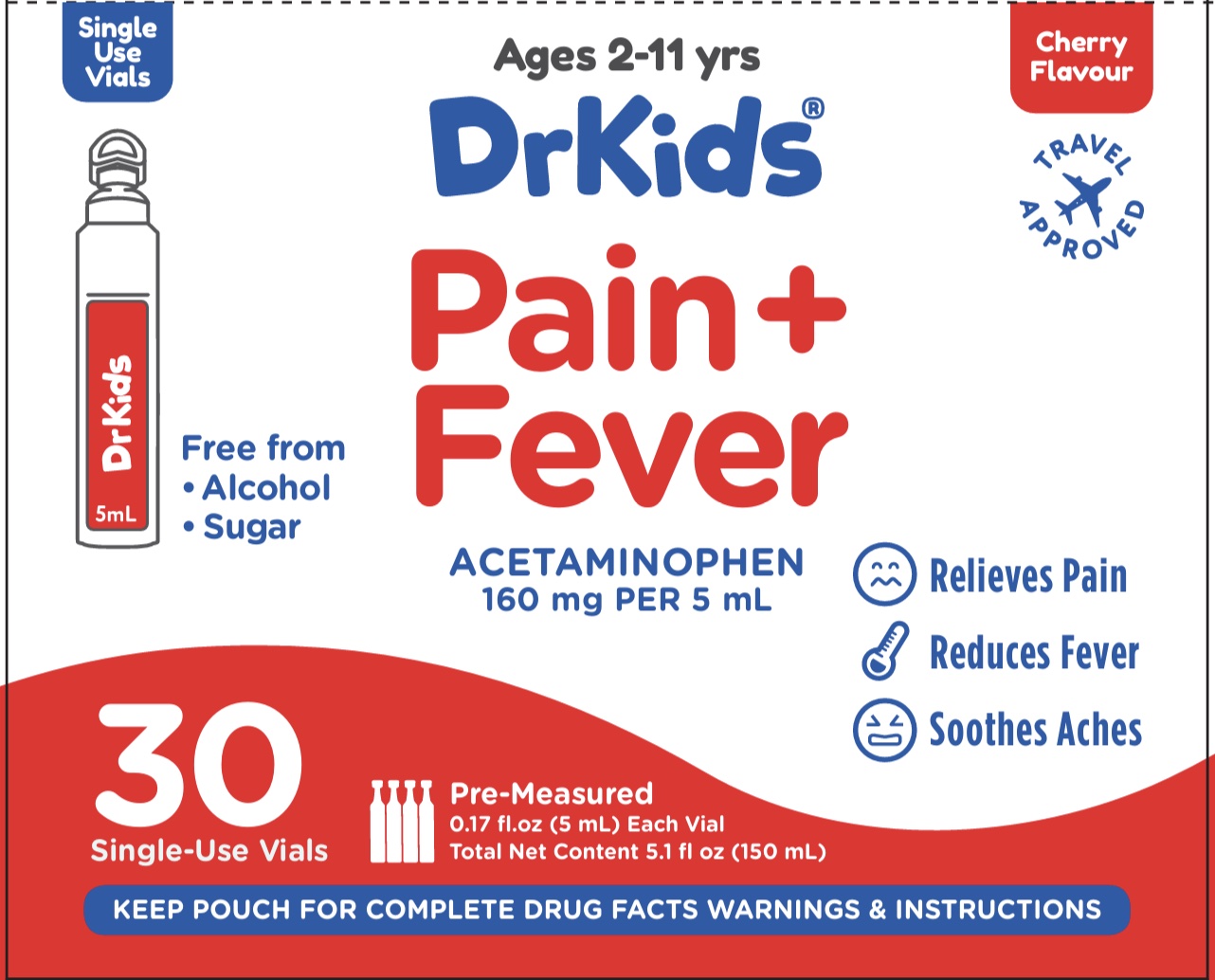 DRUG LABEL: Dr Kids
NDC: 73282-2522 | Form: SOLUTION
Manufacturer: CalmCo LLC
Category: otc | Type: HUMAN OTC DRUG LABEL
Date: 20250224

ACTIVE INGREDIENTS: ACETAMINOPHEN 160 mg/5 mL
INACTIVE INGREDIENTS: ANHYDROUS CITRIC ACID; SUCRALOSE; SORBITOL; SODIUM BENZOATE; GLYCERIN; WATER; PROPYLENE GLYCOL; XYLITOL; CARBOXYMETHYLCELLULOSE; FD&C RED NO. 40

Dr Kids Pain+ Fever

Active Ingredient and Purpose

Active ingredient (in each 5 mL vial) | Purpose
Acetaminophen 160 mg............... | Pain reliever/fever reducer

Active ingredient (in each 5mL vial) | Purpose
Acetaminophen 160 mg..................... | Pain reliever/ fever reducer

Uses

For the temporary relief of minor aches and pains due to

- sore throat
- headache
- and to reduce fever

Warnings

Liver warning: This product contains acetaminophen. Severe liver damage may occur if your child takes more than 5 doses in 24 hours, which is the maximum daily amount for this product acetaminophen

Allergy alert: Acetaminophen may cause severe skin reactions. Symptoms may include: skin redness blisters rash

Sore throat warning: If sore throat is severe, persists for more than 2 days, is accompanied or followed by fever, headache, rash, nausea, or vomiting, consult a doctor promptly

Do not use

with any other drug containing acetaminophen (prescription or nonprescription). If you are not sure whether a drug contains acetaminophen, ask a doctor or pharmacist

Ask a doctor before use if your child has

- liver disease

Ask a doctor or pharmacist before use if your child is

taking the blood thinning drug warfarin

Stop use and ask a doctor if

- pain gets worse or lasts more than 5 days
- fever gets worse or lasts more than 3 days
- edness or swelling is present
- any new symptoms appear

Keep out of reach of children.

In case of accidental overdose, get medical help or contact a Poison Control Center right away (1-800-222-1222). Prompt medical attention is critical even if you do not notice any signs or symptoms.

Directions

- this product does not contain directions or complete warnings for adult use
- do not exceed 5 doses in a 24-hour period (see liver warning)
- follow the “Easy to Use” instructions on the pouch

corresponds to your child’s age use the dose that

Age (Years) | Dose*
under 2 | consult a doctor
2 to under 6 | 1 vial (5 mL)
6 to 11 | 2 vials (10 mL)

*dose may be repeated every 4 hours while symptoms persist, up to five times a day or as directed by a doctor.

Other information

- each 5 mL vial contains: sodium 2 mg
- store between 68-77°F (20-25°C)
- do not use if pouch or vial is punctured, torn or open

Inactive ingredients

anhydrous citric acid, carboxymethylcellulose, FD&C red #40, flavors, glycerin, propylene glycol, sodium benzoate, sorbitol, sucralose, xylitol, water

Questions or comments?

+1 941-202-3270 (M-F) 9AM-5PM EST or visit www.DrKids.com

Distributed by: CalmCo LLC, Sarasota, FL 34240